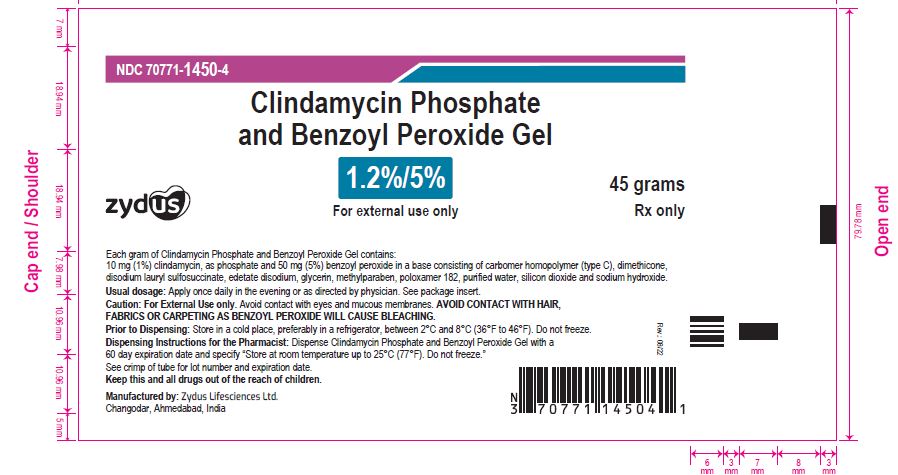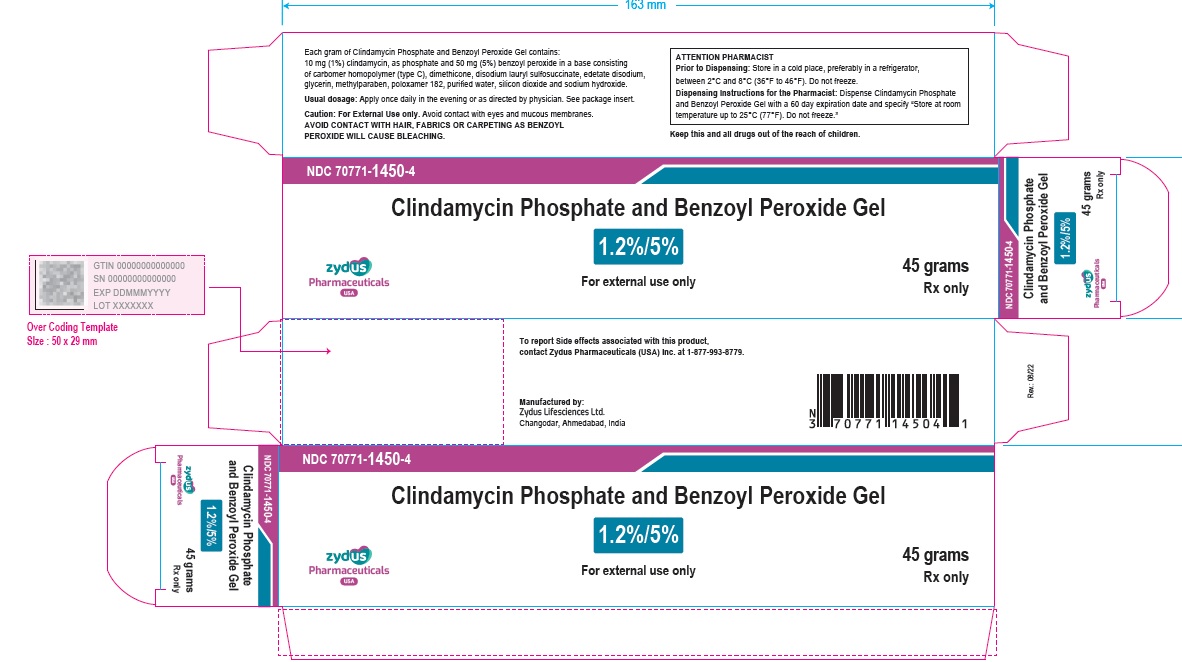 DRUG LABEL: Clindamycin Phosphate and Benzoyl Peroxide
NDC: 70771-1450 | Form: GEL
Manufacturer: Zydus Lifesciences Limited
Category: prescription | Type: HUMAN PRESCRIPTION DRUG LABEL
Date: 20241126

ACTIVE INGREDIENTS: CLINDAMYCIN PHOSPHATE 10 mg/1 g; BENZOYL PEROXIDE 50 mg/1 g
INACTIVE INGREDIENTS: CARBOMER HOMOPOLYMER TYPE C (ALLYL PENTAERYTHRITOL CROSSLINKED); DIMETHICONE; DISODIUM LAURYL SULFOSUCCINATE; EDETATE SODIUM; GLYCERIN; METHYLPARABEN; POLOXAMER 182; WATER; SILICON DIOXIDE; SODIUM HYDROXIDE

CLINDAMYCIN PHOSPHATE AND BENZOYL PEROXIDE GEL

PACKAGE LABEL.PRINCIPAL DISPLAY PANEL

NDC 70771-1450-4

Clindamycin Phosphate and Benzoyl Peroxide Gel, 1.2%/5%

Rx only

45 g